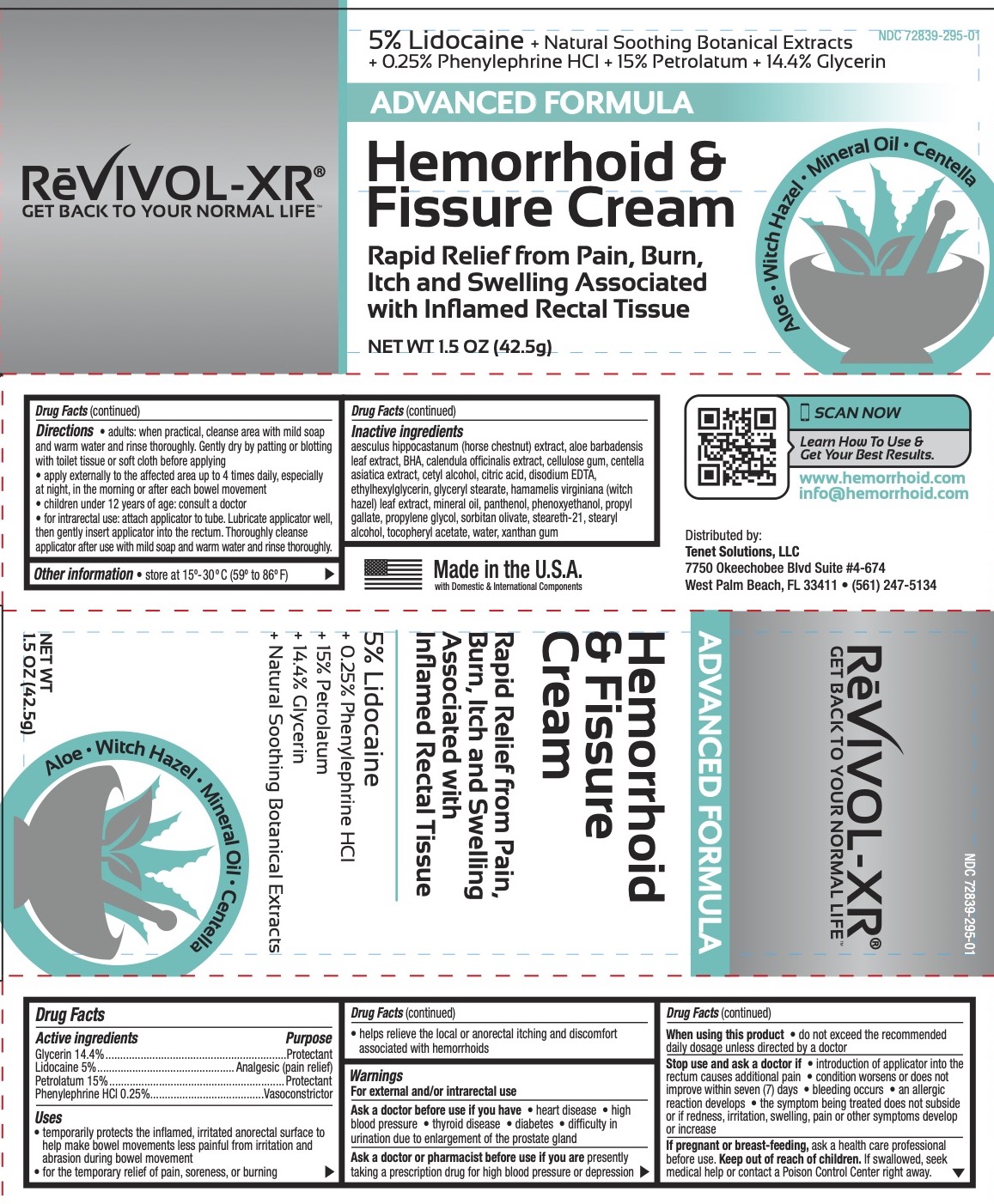 DRUG LABEL: Revivol Hemorrhoid and Fissure
NDC: 72839-295 | Form: CREAM
Manufacturer: Derma Care Research Labs, LLC
Category: otc | Type: HUMAN OTC DRUG LABEL
Date: 20241219

ACTIVE INGREDIENTS: LIDOCAINE 5 g/100 g; PETROLATUM 15 g/100 g; GLYCERIN 14.4 g/100 g; PHENYLEPHRINE HYDROCHLORIDE 0.25 g/100 g
INACTIVE INGREDIENTS: CALENDULA OFFICINALIS FLOWER; HAMAMELIS VIRGINIANA LEAF; HORSE CHESTNUT; CENTELLA ASIATICA TRITERPENOIDS; XANTHAN GUM; MINERAL OIL; PHENOXYETHANOL; .ALPHA.-TOCOPHEROL ACETATE; CETYL ALCOHOL; CITRIC ACID MONOHYDRATE; EDETATE DISODIUM; PANTHENOL; BUTYLATED HYDROXYANISOLE; ALOE VERA LEAF; SORBITAN OLIVATE; STEARETH-21; WATER; ETHYLHEXYLGLYCERIN; GLYCERYL MONOSTEARATE; PROPYL GALLATE; PROPYLENE GLYCOL; CARBOXYMETHYLCELLULOSE SODIUM; STEARYL ALCOHOL; TOCOPHEROL

Revivol Hemorrhoid and Fissure Cream

ACTIVE INGREDIENT

Glycerin 14.4%, Lidocaine 5%, Petrolatum 15%, Phenylephrine HCl 0.25%

PURPOSE

Anorectal/Hemorrhoidal

INDICATIONS AND USAGE

For the temporary relief of pain, soreness, and burning. Helps relieve the local itching and discomfort associated with hemorrhoids. Temporarily shrinks hemorrhoidal tissue. Temporarily provides a coating for the relief of anorectal discomforts. Temporarily protects the inflamed, irritated anorectal surface to help make bowel movements less painful.

WARNINGS

For external and/or intrarectal use.

Ask a doctor before use if you have: heart disease, high blood pressure, thyroid disease, diabetes, or difficulty in urination due to enlargement of the prostate gland.

Ask a doctor or pharmacist before use if you are presently taking a prescription drug for high blood pressure or depression.

When using this product do not exceed recommended dosage unless directed by a doctor.

Stop use and ask a doctor if condition worsens or does not improve within seven (7) days, bleeding occurs, an allergic reaction develops, the symptom being treated does not subside or if redness, irritation, swelling, pain or other symptoms develop or increase.

PREGNANCY OR BREAST FEEDING

Ask a health care professional before use.

KEEP OUT OF REACH OF CHILDREN

If swallowed, seek medical help or contact a Poison Control Center right away.

DOSAGE AND ADMINISTRATION

Adults: when practical, cleanse area with mild soap and warm water and rinse thoroughly. Gently dry by patting or blotting with toilet tissue or soft cloth before applying. Apply externally to the affected area up to 4 times daily, especially at night, in the morning or after each bowel movement. Children under 12 years of age: consult a doctor.

For intrarectal use: attach applicator to tube. Lubricate well, then gently insert applicator into the rectum. Thoroughly cleanse applicator after use with mild soap and warm water and rinse thoroughly.

INACTIVE INGREDIENT

Aesculus hippocastanum (horse chestnut) extract, aloe barbadensis leaf extract, BHA, calendula officinalis extract, cellulose gum, centella asiatica extract, cetyl alcohol, citric acid, disodium EDTA, ethylhexylglycerin, glyceryl stearate, hamamelis virginiana (witch hazel) leaf extract, mineral oil, panthenol, phenoxyethanol, propyl gallate, propylene glycol, sorbitan olivate, steareth-21, stearyl alcohol, tocopherol, tocopheryl acetate, water, xanthan gum.